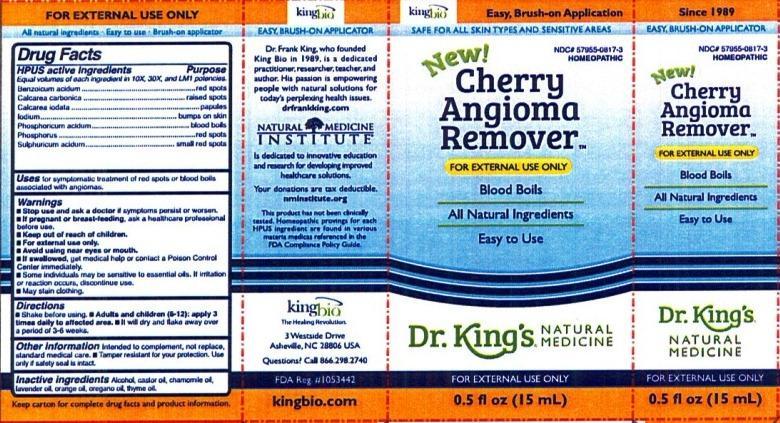 DRUG LABEL: Cherry Angioma Remover
NDC: 57955-0817 | Form: LIQUID
Manufacturer: King Bio Inc.
Category: homeopathic | Type: HUMAN OTC DRUG LABEL
Date: 20140924

ACTIVE INGREDIENTS: BENZOIC ACID 10 [hp_X]/15 mL; OYSTER SHELL CALCIUM CARBONATE, CRUDE 10 [hp_X]/15 mL; CALCIUM IODIDE 10 [hp_X]/15 mL; IODINE 10 [hp_X]/15 mL; PHOSPHORIC ACID 10 [hp_X]/15 mL; PHOSPHORUS 10 [hp_X]/15 mL; SULFURIC ACID 10 [hp_X]/15 mL
INACTIVE INGREDIENTS: ALCOHOL; CASTOR OIL; CHAMOMILE FLOWER OIL; LAVENDER OIL; ORANGE OIL; OREGANO LEAF OIL; THYME OIL

Cherry Angioma Remover™

Drug Facts

____________________________________________________________________________________________________________

HPUS active ingredients: Benzoicum acidum, Calcarea carbonica, Calcarea iodata, lodium, Phosphoricum acidum, Phosphorus, Sulphuricum acidum.

Equal volumes of each ingredient in 10X, 30X, and LM1 potencies.

INDICATIONS AND USAGE

Uses for symptomatic treatment of red spots or blood boils associated with angiomas.

Warnings

- Stop use and ask a docter if symptoms persist or worsen.
- If pregnant or breast-feeding, ask a healthcare professional before use.
- Keep out of reach of children.
- For external use only.
- Avoid using near eyes or mouth.
- If swallowed, get medical help or contact a Poison Control Center immediately.
- Some individuals may be sensitive to essential oils. If irritation or reaction occurs, discontinue use.
- May stain clothing.

- Keep out of reach of children.

Directions

- Shake before using.
- Adults and children (6-12): apply 3 times daily to affected area.
- It will dry and flake away over a period of 3-6 weeks.

Other information:

Intended to complement, not replace, standard medical care.

Tamper resistant for your protection. Use only if safety seal is intact.

INACTIVE INGREDIENT

Inactive Ingredients: Alcohol, castor oil, chamomile oil, lavender oil, orange oil, oregano oil, thyme oil.

Drug Facts

____________________________________________________________________________________________________________

HPUS active ingredients Purpose

Benzoicum acidum.............................................red spots

Calcarea carbonica.............................................raised spots

Calcarea iodata..................................................papules

lodium..............................................................bumps on skin

Phosphoricum acidum.........................................blood boils

Phosphorus.......................................................red spots

Sulphuricum acidum...........................................small red spots